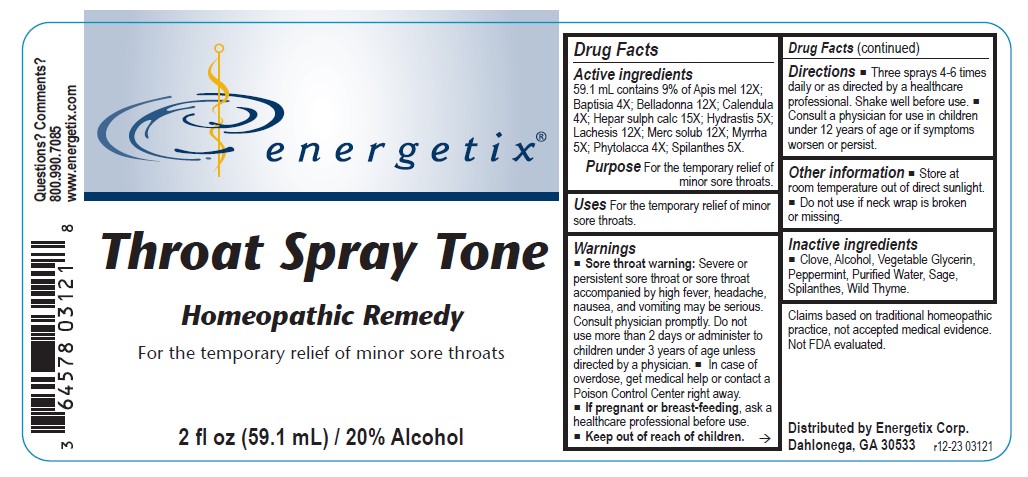 DRUG LABEL: Throat Spray- Tone
NDC: 64578-0141 | Form: LIQUID
Manufacturer: Energetix Corporation
Category: homeopathic | Type: HUMAN OTC DRUG LABEL
Date: 20241211

ACTIVE INGREDIENTS: APIS MELLIFERA 12 [hp_X]/59.1 mL; BAPTISIA TINCTORIA 4 [hp_X]/59.1 mL; ATROPA BELLADONNA 12 [hp_X]/59.1 mL; CALENDULA OFFICINALIS FLOWERING TOP 4 [hp_X]/59.1 mL; CALCIUM SULFIDE 15 [hp_X]/59.1 mL; GOLDENSEAL 5 [hp_X]/59.1 mL; LACHESIS MUTA VENOM 12 [hp_X]/59.1 mL; MERCURIUS SOLUBILIS 12 [hp_X]/59.1 mL; MYRRH 5 [hp_X]/59.1 mL; PHYTOLACCA AMERICANA ROOT 4 [hp_X]/59.1 mL; ACMELLA OLERACEA FLOWERING TOP 5 [hp_X]/59.1 mL
INACTIVE INGREDIENTS: ALCOHOL; WATER; GLYCERIN; THYMUS SERPYLLUM; CLOVE; MENTHA PIPERITA; SAGE; ACMELLA OLERACEA FLOWER

Throat Spray Tone

ACTIVE INGREDIENT

Active ingredients 59.1 mL contains 9% of: Apis mel 12X; Baptisia 4X; Belladonna 12X; Calendula officinalis 4X; Hepar sulph calc 15X; Hydrastis 5X; Lachesis 12X; Merc solub 12X; Myrrha 5X; Phytolacca 4X; Spilanthes 5X.

Claims based on traditional homeopathic practice, not accepted medical evidence. Not FDA evaluated.

INDICATIONS AND USAGE

UsesFor the temporary relief of minor sore throats.

Warnings

- Sore throat warning:Severe or persistent sore throat or sore throat accompanied by high fever, headache, nausea, and vomiting may be serious. Consult physician promptly. Do not use more than 2 days or administer to children under 3 years of age unless directed by a physician.
- In case of overdose, get medical help or contact a Poison Control Center right away.
- If pregnant or breast feeding, ask a healthcare professional before use.

- Keep out of reach of children.

Directions

- Three sprays 4-6 times daily or as directed by a healthcare professional. Shake well before use.
- Consult a physician for use in children under 12 years of age or if symptoms worsen or persist.

Other information

- Store at room temperature out of direct sunlight.
- Do not use if neck wrap is broken or missing.

Inactive ingredients

- Clove, Alcohol, Vegetable Glycerin, Peppermint, Purified Water, Sage, Spilanthes, Wild Thyme.

QUESTIONS

Distributed by

Energetix Corp.

Dahlonega, GA 30533

Questions? Comments?

800.990.7085

www.energetix.com

PACKAGE LABEL

energetix

Throat Spray Tone

Homeopathic Remedy

For the temporary relief of minor sore throats.

2 fl oz (59.1 mL) / 20% Alcohol

PURPOSE

PurposeFor the temporary relief of minor sore throats.